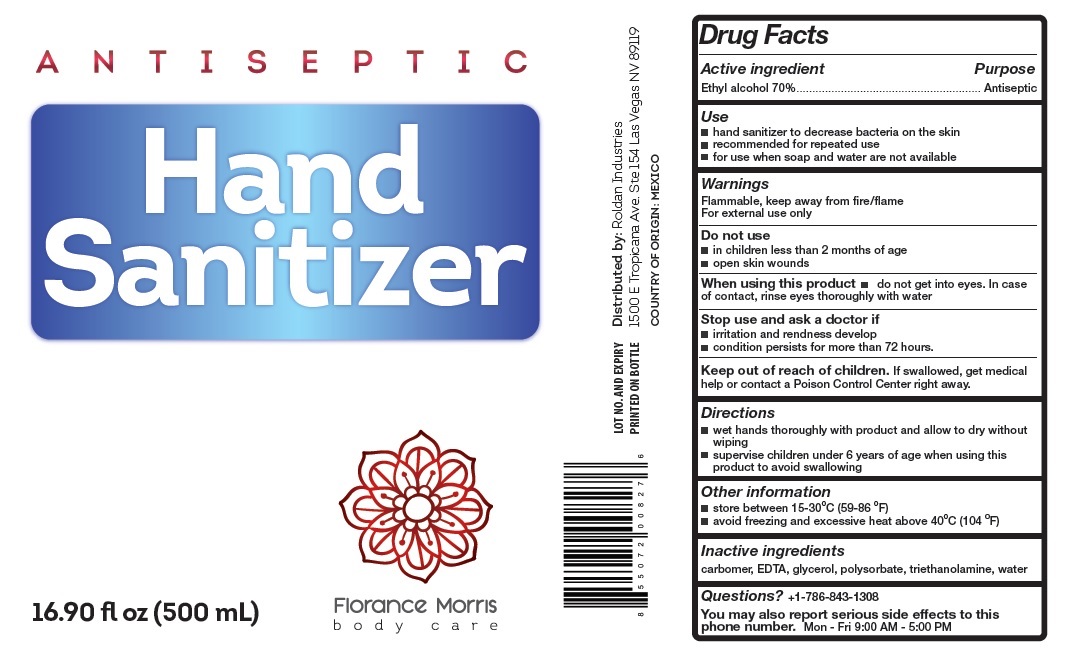 DRUG LABEL: Florance Morris ANTISEPTIC Hand Sanitizer
NDC: 79109-170 | Form: GEL
Manufacturer: ROLDAN INDUSTRIES
Category: otc | Type: HUMAN OTC DRUG LABEL
Date: 20200815

ACTIVE INGREDIENTS: ALCOHOL 70 mL/100 mL
INACTIVE INGREDIENTS: CARBOMER HOMOPOLYMER, UNSPECIFIED TYPE; EDETIC ACID; GLYCERIN; POLYSORBATE 20; TROLAMINE; WATER

Florance Morris ANTISEPTIC Hand Sanitizer

Active ingredient

Ethyl alcohol 70%

Purpose

Antiseptic

Use

- hand sanitizer to decrease bacteria on the skin
- recommended for repeated use
- for use when soap and water are not available

Warnings

Flammable, keep away from fire/flame
For external use only
Do not use

- in children less than 2 months of age
- open skin wounds

When using this product • do not get into eyes. In case of contact, rinse eyes thoroughly with water
Stop use and ask a doctor if

- irritation and redness develop
- condition persists for more than 72 hours.

Keep out of reach of children.

If swallowed, get medical help or contact a Poison Control Center right away.

Directions

- wet hands thoroughly with product and allow to dry without wiping
- supervise children under 6 years of age when using this product to avoid swallowing

Other information

- store between 15-30˚C (59-86˚F)
- avoid freezing and excessive heat above 40˚C (104˚F)

Inactive ingredients

carbomer, EDTA, glycerol, polysorbate, triethanolamine, water

Questions?

+1-786-843-1308
You may also report serious side effects to this phone number. Mon - Fri 9:00 AM - 5:00 PM

Distributed by: Roldan Industries
1500 E Tropicana Ave. Ste 154 Las Vegas NV 89119

COUNTRY OF ORIGIN: MEXICO